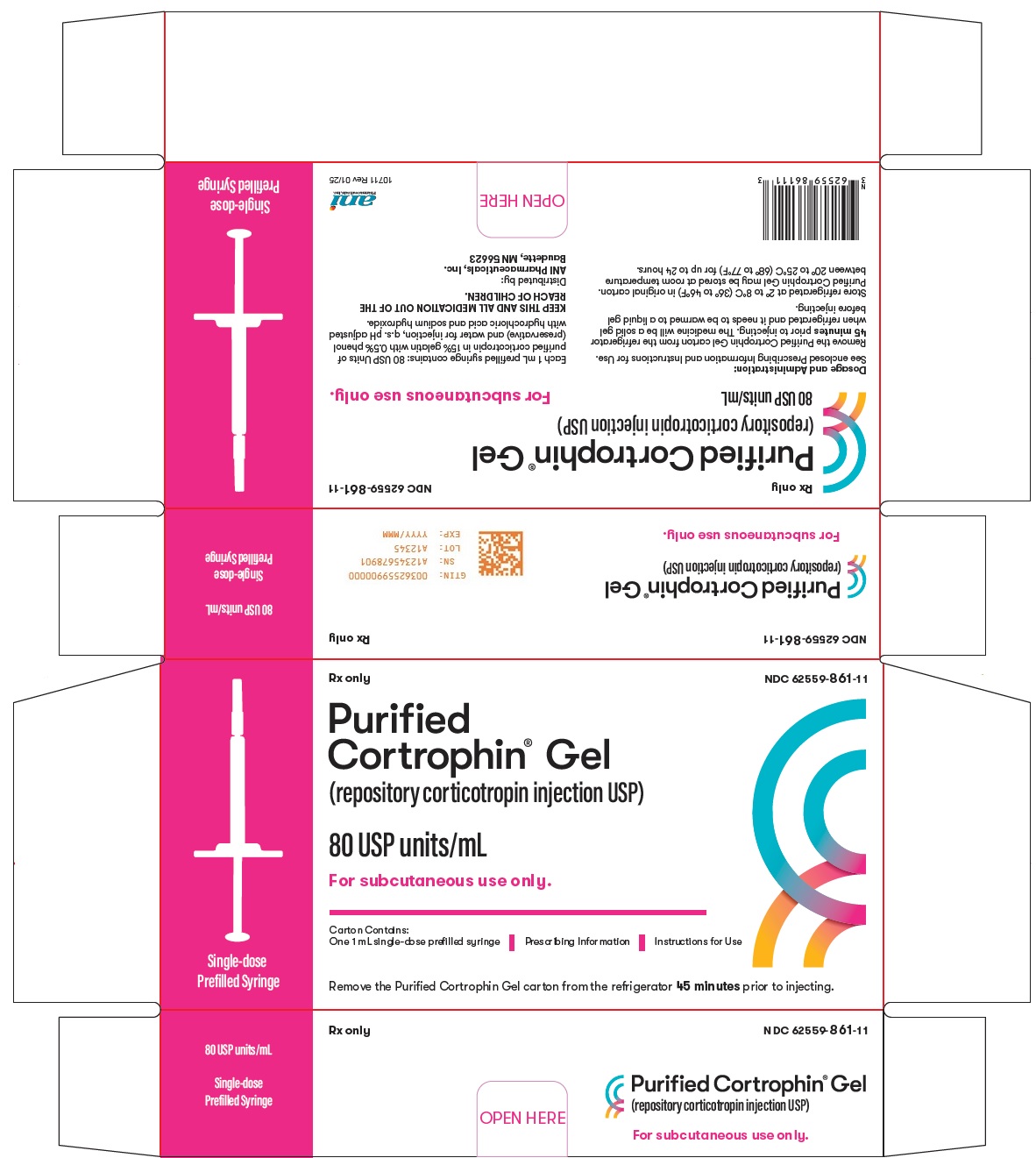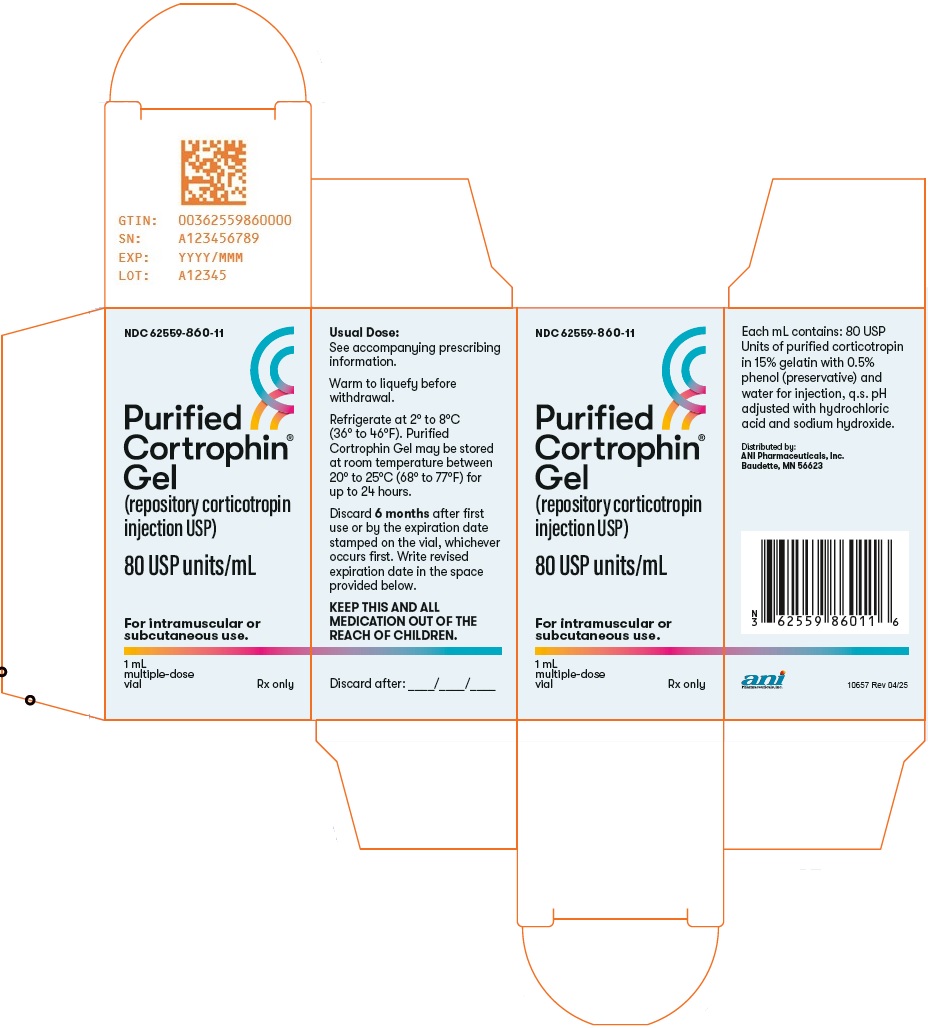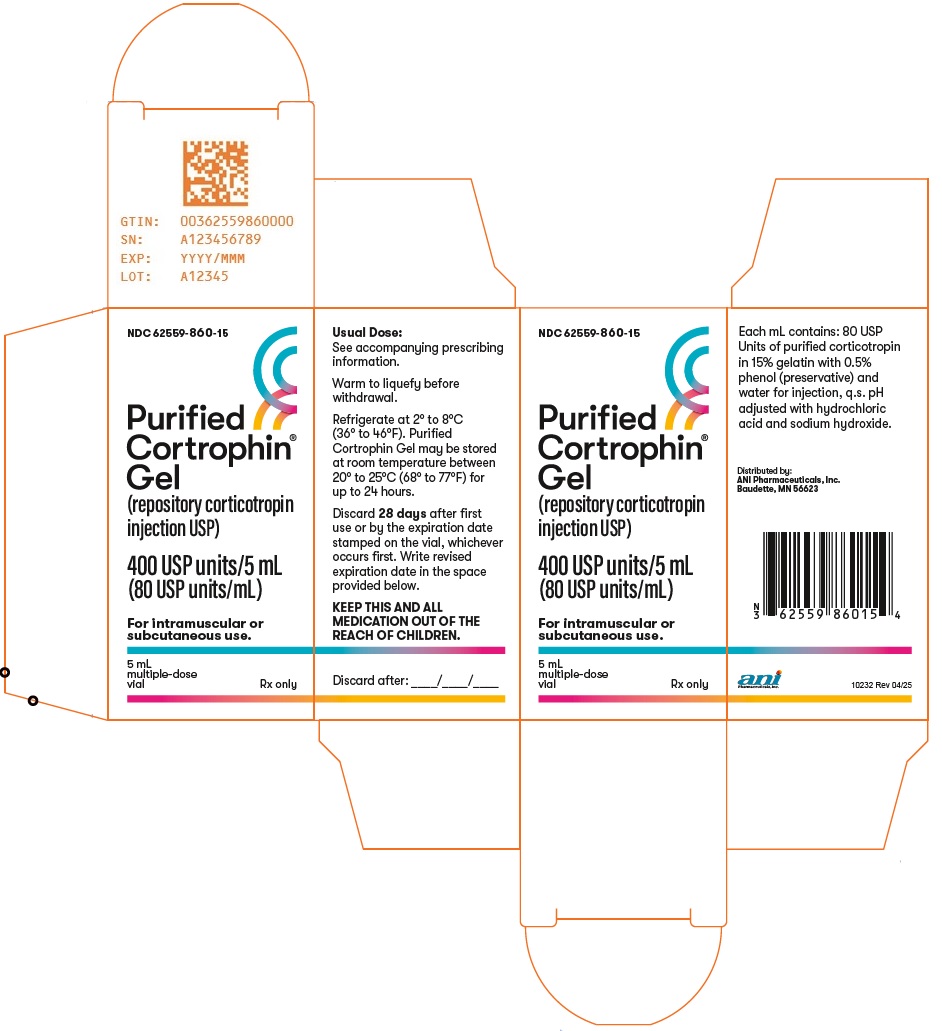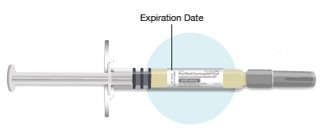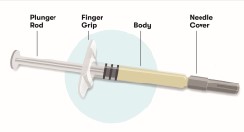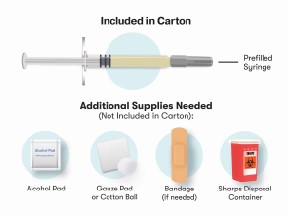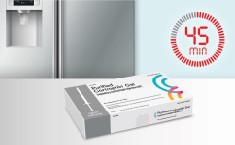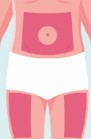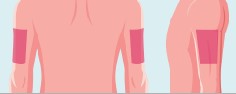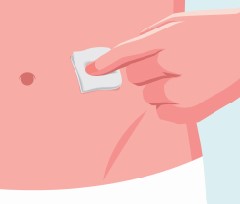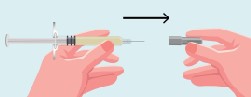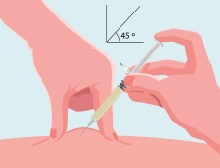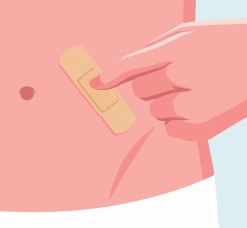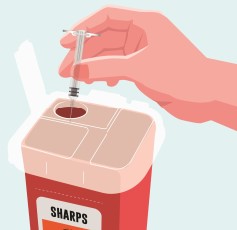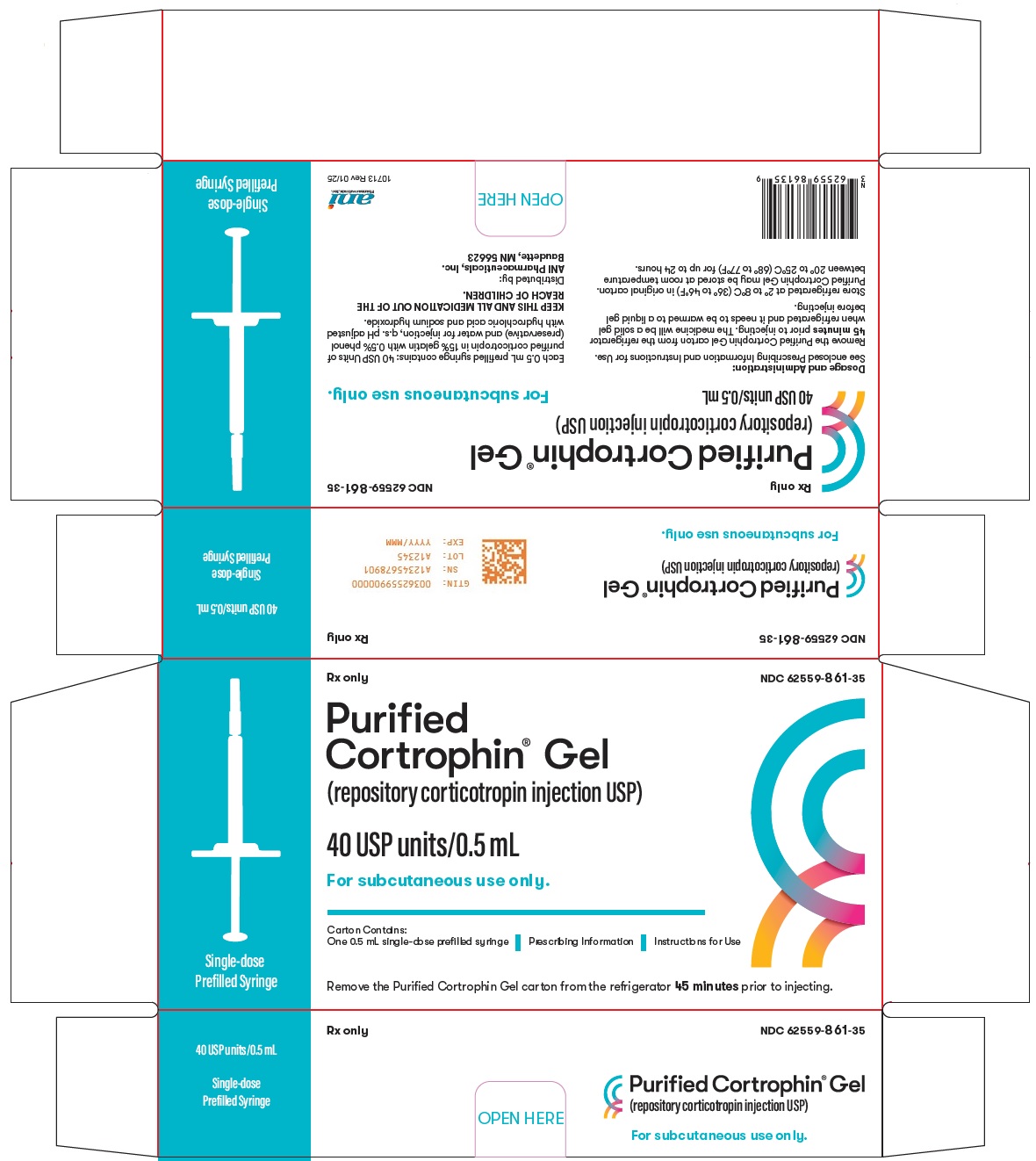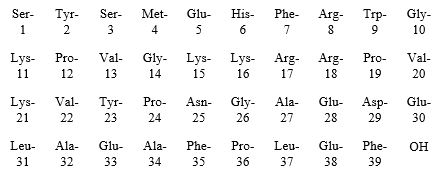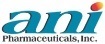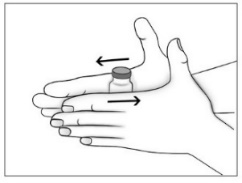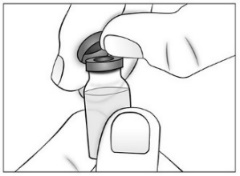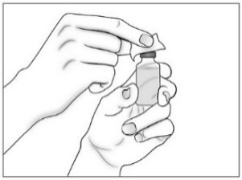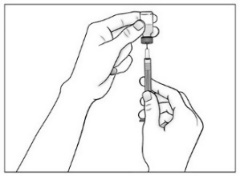 DRUG LABEL: Purified Cortrophin Gel
NDC: 62559-860 | Form: INJECTION
Manufacturer: ANI Pharmaceuticals, Inc.
Category: prescription | Type: HUMAN PRESCRIPTION DRUG LABEL
Date: 20260209

ACTIVE INGREDIENTS: CORTICOTROPIN 80 [USP'U]/1 mL
INACTIVE INGREDIENTS: GELATIN, UNSPECIFIED; PHENOL; WATER; SODIUM HYDROXIDE; HYDROCHLORIC ACID

PURIFIED CORTROPHIN® GEL
(Repository Corticotropin Injection USP)
Rx only

DESCRIPTION

Purified Cortrophin Gel is a porcine derived purified corticotropin (ACTH) in a sterile solution of gelatin. It is made up of a complex mixture of ACTH, ACTH related peptides and other porcine pituitary derived peptides.

The drug product is a sterile preparation containing 80 USP units per mL and it contains 0.5% phenol (as preservative), 15.0% gelatin (for prolonged activity), water for injection, and the pH is adjusted with hydrochloric acid and sodium hydroxide.

Purified Cortrophin Gel contains the porcine derived ACTH (1-39) with the following amino acid sequence:

CLINICAL PHARMACOLOGY

Purified Cortrophin Gel is the anterior pituitary hormone which stimulates the functioning adrenal cortex to produce and secrete adrenocortical hormones.

Following administration of a single intramuscular injection of 80 Units of Cortrophin Gel to healthy volunteers (n=20) in an open label pharmacodynamic study, the median time (range) to reach peak cortisol concentration was 8 (3-12) hours. The baseline corrected geometric mean maximum (CV%) cortisol levels were 34.52 µg/dL (28.2%).

INDICATIONS AND USAGE

Purified Cortrophin Gel is indicated in the following disorders:

1. Rheumatic disorders:

As adjunctive therapy for short-term administration (to tide the patient over an acute episode or exacerbation) in:
  Psoriatic arthritis.
  Rheumatoid arthritis, including juvenile rheumatoid arthritis (selected cases may require low-dose maintenance therapy).
  Ankylosing spondylitis.
  Acute gouty arthritis.

2. Collagen diseases:

During an exacerbation or as maintenance therapy in selected cases of:
  Systemic lupus erythematosus.
  Systemic dermatomyositis (polymyositis).

3. Dermatologic diseases:

Severe erythema multiforme (Stevens-Johnson syndrome).
  Severe psoriasis.

4. Allergic states:

Atopic dermatitis
  Serum sickness.

5. Ophthalmic diseases:

Severe acute and chronic allergic and inflammatory processes involving the eye and its adnexa such as:
  Allergic conjunctivitis.
  Keratitis.
  Iritis and iridocyclitis.
  Diffuse posterior uveitis and choroiditis.
  Optic neuritis.
  Chorioretinitis.
  Anterior segment inflammation.

6. Respiratory diseases:

Symptomatic sarcoidosis.

7. Edematous states:

To induce a diuresis or a remission of proteinuria in the nephrotic syndrome without uremia of the idiopathic type or that due to lupus erythematosus.

8. Nervous system:

Acute exacerbations of multiple sclerosis.

CONTRAINDICATIONS

Purified Cortrophin Gel is contraindicated for intravenous administration.

Purified Cortrophin Gel is contraindicated in patients with scleroderma, osteoporosis, systemic fungal infections, ocular herpes simplex, recent surgery, history of or the presence of a peptic ulcer, congestive heart failure, hypertension, or sensitivity to proteins derived from porcine sources.

Purified Cortrophin Gel is contraindicated in patients with primary adrenocortical insufficiency or adrenocortical hyperfunction.

WARNINGS

Chronic administration of corticotropin may lead to adverse effects which are not reversible.

This product should not be administered for treatment until adrenal responsiveness has been verified with the route of administration which will be utilized during treatment, intramuscularly or subcutaneously. A rise in urinary and plasma corticosteroid values provides direct evidence of a stimulatory effect. Although the action of corticotropin is similar to that of exogenous adrenocortical steroids the quantity of adrenocorticoid may be variable. In patients who receive prolonged corticotropin therapy the additional use of rapidly acting corticosteroids before, during and after an unusual stressful situation is indicated.

Masking Symptoms of Other Diseases

Corticotropin may only suppress symptoms and signs of chronic disease without altering the natural course of the disease.

Immunogenicity Potential

Purified Cortrophin Gel is immunogenic. Limited available data suggest that a patient may develop antibodies to Purified Cortrophin Gel after chronic administration and loss of endogenous ACTH and Purified Cortrophin Gel activity. Prolonged administration of Purified Cortrophin Gel may increase the risk of hypersensitivity reactions. Cases of anaphylaxis following administration have also been reported in the postmarketing setting. Sensitivity to porcine protein should be considered before starting therapy and during the course of treatment should symptoms arise.

Ophthalmic Effects

Prolonged use of corticotropin may produce posterior subcapsular cataracts and glaucoma with possible damage to the optic nerves.

Infections

Corticotropin may mask some signs of infection, and new infections including those of the eye due to fungi or viruses may appear during its use. There may be decreased resistance and inability to localize infection when corticotropin is used.

Elevated Blood Pressure, Salt and Water Retention, and Hypokalemia

Corticotropin can cause elevation of blood pressure, salt and water retention, and increased excretion of potassium. Dietary salt restriction and potassium supplementation may be necessary. Corticotropin increases calcium excretion.

Vaccination

While on corticotropin therapy, patients should not be vaccinated against smallpox. Other immunization procedures should be undertaken with caution in patients who are receiving corticotropin, especially when high doses are administered because of the possible hazards of neurological complications and lack of antibody response.

PRECAUTIONS

General

Patients with latent tuberculosis or tuberculin reactivity who receive corticotropin should be closely observed as reactivation of the disease may occur. During prolonged corticotropin therapy, these patients should receive chemoprophylaxis.

Skin testing should be performed prior to treatment of all patients with suspected sensitivity to porcine protein. Immediately following intramuscular or subcutaneous administration of corticotropin all patients should be observed carefully for sensitivity reactions.

Relative adrenocortical insufficiency induced by prolonged corticotropin therapy may be minimized by gradual reduction of corticotropin dosage. This type of insufficiency may persist for months after discontinuation of therapy; therefore, in any situation of stress during that period, hormone therapy should be reinstituted.

There is an enhanced effect of corticotropin in patients with hypothyroidism and in those with cirrhosis.

The lowest possible dosage of corticotropin should be used to control the condition under treatment, and when reduction in dosage is possible the reduction should be gradual.

Corticotropin should be administered for treatment only when the disease is intractable to more conventional therapy. Corticotropin should be adjunctive and not the sole therapy in the treatment of a disease.

Since maximal corticotropin stimulation of the adrenals may be limited during the first few days of treatment, other drugs should be administered when an immediate therapeutic effect is desirable.

When infection is present appropriate anti-infective therapy should be administered during corticotropin and following discontinuation of corticotropin therapy.

Treatment of acute gouty arthritis should be limited to a few days. Since rebound attacks may occur when corticotropin is discontinued, conventional concomitant therapy should be administered during corticotropin treatment, and for several days after it is stopped.

Psychic derangements may appear when corticotropin is used, ranging from euphoria, insomnia, mood swings, personality changes, and depression, to frank psychotic manifestations. Also, existing emotional instability or psychotic tendencies may be aggravated by corticotropin.

Corticotropin should be used with caution in patients with diabetes, abscess, pyogenic infections, diverticulitis, renal insufficiency, and myasthenia gravis.

Growth and development of infants and children on prolonged corticotropin therapy should be carefully observed.

Although controlled clinical trials have shown ACTH to be effective in speeding the resolution of acute exacerbations of multiple sclerosis, they do not show that it affects the ultimate outcome or natural history of the disease.

Since complications of treatment with ACTH are dependent on the size of the dose and the duration of treatment, a risk/benefit decision must be made in each individual case as to dose and duration of treatment.

Drug Interactions

Aspirin should be used cautiously in conjunction with corticotropin in hypoprothrombinemia.

Pregnancy

Since fetal abnormalities have been observed in experimental animals, use of this drug in pregnancy, nursing mothers, or women of childbearing potential requires that the potential benefits of the drug be weighed against the potential hazards to the mother and embryo or fetus. Infants born of mothers who have received substantial doses of corticotropin during pregnancy should be carefully observed for signs of hypoadrenalism.

ADVERSE REACTIONS

Fluid and Electrolyte Disturbances
Sodium retention.
Hypokalemic alkalosis.
Fluid retention.
Calcium loss.
Potassium loss.

Musculoskeletal
Muscle weakness.
Loss of muscle mass.
Steroid myopathy.
Osteoporosis.
Vertebral compression fractures.
Aseptic necrosis of femoral and humeral heads.
Pathologic fracture of long bones.

Gastrointestinal
Peptic ulcer with possible perforation and hemorrhage.
Abdominal distention.
Ulcerative esophagitis.
Pancreatitis.

Dermatologic
Injection site reactions.
Impaired wound healing.
Increased sweating.
Thin fragile skin.
Suppression of skin test reactions.
Petechiae and ecchymoses.
Acne.
Hyperpigmentation.
Facial erythema.

Cardiovascular
Hypertension.
Congestive heart failure.
Necrotizing angiitis.

Neurological
Convulsions.
Increased intracranial pressure with papilledema (pseudo-tumor cerebri), usually after treatment.
Headache.
Vertigo.

Endocrine
Menstrual irregularities.
Development of Cushingoid state.
Suppression of growth in children.
Secondary adrenocortical and pituitary insufficiency, particularly in times of stress, as in trauma, surgery or illness.
Decreased carbohydrate tolerance.
Manifestations of latent diabetes mellitus.
Increased requirements for insulin or oral hypoglycemic agents in diabetics.
Hirsutism.

Ophthalmic
Posterior subcapsular cataracts.
Increased intraocular pressure.
Glaucoma with possible damage to optic nerve.
Exophthalmos.

Metabolic
Negative nitrogen balance due to protein catabolism.

Allergic reactions
Allergic reactions manifesting as dizziness, nausea and vomiting, skin reactions, anaphylaxis (anaphylactic shock, urticaria, respiratory compromise, edema), especially in patients with allergic responses to proteins.

Miscellaneous
Weight gain.
Abscess.
Development of antibodies and loss of stimulatory effect.

To report SUSPECTED ADVERSE REACTIONS, contact ANI Pharmaceuticals, Inc. at 1-800-308-6755 or FDA at 1-800-FDA-1088 or www.fda.gov/medwatch.

DOSAGE AND ADMINISTRATION

Standard tests for verification of adrenal responsiveness to corticotropin may utilize as much as 80 units as a single injection or one or more injections of a lesser dosage. Verification tests should be performed prior to treatment with corticotropins. The test should utilize the route(s) of administration proposed for treatment. Following verification dosage should be individualized according to the disease under treatment and the general medical condition of each patient. Frequency and dose of the drug should be determined by considering severity of the disease, plasma and urine corticosteroid levels and the initial response of the patient. Only gradual change in dosage schedules should be attempted, after full drug effects have become apparent.

This product may be administered subcutaneously or intramuscularly with the vial and subcutaneously with the prefilled syringe.

In the treatment of acute exacerbations of multiple sclerosis daily subcutaneous or intramuscular doses of 80-120 units for 2-3 weeks.

The chronic administration of more than 40 units daily may be associated with uncontrollable adverse effects.

When reduction in dosage is indicated this should be accomplished gradually by either reducing the amount of each injection, or administering injections at longer intervals, or by a combination of both of the above. During reduction of dosage, careful consideration should be given to the disease being treated, the general medical condition of the patient and the duration over which corticotropin was administered.

Important Administration Instructions

- Parenteral drug products should be inspected visually for particulate matter and discoloration prior to administration whenever solution and container permit. Purified Cortrophin Gel is a clear, light amber liquid gel at room temperature. Do not use if the solution is discolored or cloudy or the solution contains particulate matter.
- Purified Cortrophin Gel will be a solid gel when refrigerated and needs to be warmed to a liquid gel before administration.
  - For Purified Cortrophin Gel vials warm by rolling between your hands for a few minutes.
  - For Purified Cortrophin Gel prefilled syringes remove the carton from the refrigerator and leave at room temperature for 45 minutes.
- The recommended injection sites include abdomen, upper thigh, or upper arm. Do not inject within 2 inches of navel.

Information for Patients

Advise patients and/or caregivers to read the FDA-approved patient information (Instructions for Use).

HOW SUPPLIED/ STORAGE AND HANDLING

Purified Cortrophin Gel is a clear, light amber liquid gel at room temperature. It is supplied sterile in:

- Multiple-dose vials for intramuscular or subcutaneous use

Package Size | Total Volume | NDC
1 mL multiple-dose vial | 80 USP units/mL | 62559-860-11
5 mL multiple-dose vial | 400 USP units/5 mL | 62559-860-15

- Single-dose prefilled syringes for subcutaneous use only

Package Size | Total Volume | NDC
0.5 mL single-dose prefilled syringe | 40 USP units/0.5 mL | 62559-861-35
1 mL single-dose prefilled syringe | 80 USP units/mL | 62559-861-11

Storage

Store Purified Cortrophin Gel vials and prefilled syringes refrigerated at 2° to 8°C (36° to 46°F).

Purified Cortrophin Gel vials and prefilled syringes may be stored at room temperature between 20° to 25°C (68° to 77°F) for up to 24 hours.

After first use discard Purified Cortrophin Gel vials per the table below. Write the revised expiration date in the space provided on the carton labeling.

Package Size | Discard By
1 mL multiple-dose vial | 6 months after first use or by the expiration date stamped on the vial, whichever occurs first.
5 mL multiple-dose vial | 28 days after first use or by the expiration date stamped on the vial, whichever occurs first.

Discard Purified Cortrophin Gel prefilled syringes immediately after use or by the expiration date stamped on the syringe.

Distributed by:
ANI Pharmaceuticals, Inc.
Baudette, MN 56623

10233 Rev 08/25
10716 Rev 08/25

Instructions for Use

Purified Cortrophin® Gel
(Repository Corticotropin Injection USP)
for intramuscular or subcutaneous use

This Instructions for Use contains information on how to inject Purified Cortrophin Gel.

Your healthcare provider should show you how to prepare and inject Purified Cortrophin Gel the right way before you inject it for the first time. Do not try to inject yourself until you have been shown the right way to give your injections by your healthcare provider.

Important information about how to inject Purified Cortrophin Gel

- Purified Cortrophin Gel is given as an injection into the muscle or under the skin as directed by your healthcare provider. Do not inject it into a vein or take by mouth.
- Inject Purified Cortrophin Gel exactly as your healthcare provider tells you. Your healthcare provider will tell you where to give the injection, how much to give, how often and when to give it.
- Do not use Purified Cortrophin Gel until your healthcare provider has taught you how to give the injection.

Before starting, collect all of the supplies that you will need to use for preparing and injecting Purified Cortrophin Gel. You will need the following supplies:

- Vial of Purified Cortrophin Gel
- Syringe
- Needle for withdrawal (20G or as prescribed by your healthcare provider)
- Needle for injection (23G or as prescribed by your healthcare provider)
- 2 alcohol pads
- Cotton balls or gauze pad
- Bandage (if needed)
- Sharps container for throwing away used syringes and needles (see “Disposing of used needles and syringes”)

Preparing Purified Cortrophin Gel

- Wash your hands well and dry with a clean towel.
- Remove the vial from the refrigerator. Check the expiration date on the vial. Do not use if the expiration date has passed.
- Purified Cortrophin Gel will be a solid gel when refrigerated and it needs to be warmed to a liquid gel before injecting. Warm the solid gel in the vial by rolling between your hands for a few minutes. Do not microwave or heat on the stove.
- Remove (flip off) the plastic cap from the top of the Purified Cortrophin Gel vial and throw it away in the trash. Do not put the plastic cap back on the vial.
- Wipe the top of the vial rubber stopper with a new sterile alcohol pad.
- Use a new sterile 20G needle (or needle prescribed for withdrawal) and syringe to draw up the amount of Purified Cortrophin Gel your healthcare provider has told you to use.

Injecting Purified Cortrophin Gel

- Prepare the skin where you are going to give the injection by wiping it with a new sterile alcohol pad. Allow to air dry.
- Replace the 20G needle (or needle prescribed for withdrawal) used for drawing the Purified Cortrophin Gel from the vial with the 23G needle (or needle prescribed for injection). Do not use the 20G needle for injecting.
- Give the injection the way your healthcare provider has instructed you.
- There may be a little bleeding at the injection site. You can press a cotton ball or gauze pad over the injection site (do not rub).
- If needed, you may cover the injection site with a bandage.
- Return the vial to the refrigerator as soon as possible.

Disposing of your used needles and syringe

- Put your used needles and syringe in an FDA-cleared sharps disposal container right away after use. Do not throw away (dispose of) your used needles and syringe in your household trash.
- If you do not have an FDA-cleared sharps disposal container, you may use a household container that is:
  - made of a heavy-duty plastic,
  - can be closed with a tight-fitting, puncture-resistant lid, without sharps being able to come out,
  - upright and stable during use,
  - leak-resistant, and
  - properly labeled to warn of hazardous waste inside the container.
- When your sharps disposal container is almost full, you will need to follow your community guidelines for the right way to dispose of your sharps disposal container. There may be state or local laws about how you should throw away used needles and syringes. For more information about safe sharps disposal, and for specific information about sharps disposal in the state that you live in, go to the FDA’s website at: http://www.fda.gov/safesharpsdisposal.
- Do not dispose of your used sharps disposal container in your household trash unless your community guidelines permit this. Do not recycle your used sharps disposal container.

Storing Purified Cortrophin Gel

- Store vials of Purified Cortrophin Gel in the refrigerator between 36°F to 46°F (2°C to 8°C).
- 1 mL vials: Throw away (discard) any 1 mL vials 6 months after first use or by the expiration date printed on the label, whichever occurs first.
- 5 mL vials: Throw away (discard) any 5 mL vials 28 days after first use or by the expiration date printed on the label, whichever occurs first.
- Write the revised discard by date in the space provided on the carton labeling.

Keep Purified Cortrophin Gel and all medicines out of the reach of children.

Distributed by: ANI Pharmaceuticals, Inc., Baudette, MN 56623

This Instructions for Use has been approved by the U.S. Food and Drug Administration.

Revised: October 2023

Instructions for Use

PURIFIED CORTROPHIN GEL
(Repository Corticotropin Injection USP)

40 USP units/0.5 mL and 80 USP units/mL
Single-dose prefilled syringe

For Subcutaneous Use Only

This Instructions for Use contains information on how to prepare and inject Purified Cortrophin Gel prefilled syringe.

Your healthcare provider should show you how to prepare and inject Purified Cortrophin Gel the right way before you inject it for the first time. Do not try to inject yourself until you have been shown the right way to give your injections by your healthcare provider.

Purified Cortrophin Gel prefilled syringe (see Figure A).

Figure A

Important information you need to know before injecting Purified Cortrophin Gel

- Read all of this Instructions for Use carefully before using the Purified Cortrophin Gel prefilled syringe.
- Purified Cortrophin Gel is given as an injection directly under the skin as directed by your healthcare provider.
  - Do not inject it into a vein or take by mouth.
- Inject Purified Cortrophin Gel exactly as your healthcare provider tells you. Your healthcare provider will tell you where to give the injection, how much to give, how often, and when to give it.
  - You may need more than 1 injection based on your prescribed dose.
- Do not use Purified Cortrophin Gel until your healthcare provider has shown you how to give the injection.
- Do not use if the tamper evident seal is torn, loose, or not present.
- Do not use the Purified Cortrophin Gel prefilled syringe if it has been dropped on a hard surface or damaged.

1. Collect your supplies

- Use a clean, flat surface, such as a table.
- You will need (see Figure B):
  - 1 Purified Cortrophin Gel prefilled syringe (see Figure A)
  - 1 alcohol pad
  - 1 cotton ball or gauze pad
  - 1 bandage (if needed)
  - Sharps container for throwing away used syringes and needles (see “Disposing of your used prefilled syringes and needles”)

Figure B

2. Preparing the prefilled syringe

- Remove the carton from the refrigerator and place on a clean surface for 45 minutes to let the prefilled syringe warm up to room temperature 68°F to 77°F (20°C to 25°C) (see Figure C).
  - Purified Cortrophin Gel will be a solid gel when refrigerated and it needs to be warmed to a liquid gel before injecting.
  - Remove the prefilled syringe by the syringe body only. Do not remove the prefilled syringe by the plunger rod or needle cover.
  - Do not remove the needle cover while allowing the prefilled syringe to reach room temperature.
  - Do not warm the prefilled syringe in any other way. For example, do not microwave or heat on the stove.
  - Do not use the prefilled syringe if the gel in the syringe still appears to be solid.

Figure C

3. Check your medicine

- Check the expiration date on the syringe label (see Figure D). Do not use if expiration date has passed.
- Make sure that you have the right dose as prescribed to you by your healthcare provider. Your dose may require more than 1 injection.
- Check that the liquid gel in the syringe is light amber (yellow) in color. Do not use if the gel appears cloudy or has particles in it. Throw it away (discard) and get a new syringe.
- It is ready to be used when the medicine is a liquid gel and not a solid gel.

Figure D

4. Selecting an injection site

- Wash your hands well and dry with a clean towel.
- Choose an injection site on the stomach (abdomen) area or upper thigh (see Figure E).
  - Do not inject within 2 inches of the belly button (navel).
- Do not inject in areas where the skin is red, swollen, irritated, inflamed tender, bruised, scaly, hard, or has scars or stretch marks.

Figure E

- If someone else is giving you the injection, it can also be injected in the side and back of the upper arm (see Figure F).

Figure F

5. Injecting Purified Cortrophin Gel

- Clean the injection site with an alcohol pad (see Figure G). Allow to air dry.

Figure G

- Hold the syringe by the body with one hand.
  - Do not move or pull back on the plunger.
- Remove the needle cover with the other hand and throw it away (discard) (see Figure H).
  - Do not touch the needle.
  - Do not recap the needle.
  - You may see a drop of liquid at the end of the needle. This is normal.

Figure H

- With one hand, gently pinch the area of the cleaned skin and hold it firmly (see Figure I).
- Insert the needle into the pinched skin at a 45-degree angle (see Figure I).
- Release the pinched skin and slowly push down the plunger until all the medicine has been injected.
- Pull the needle out of the skin while keeping the syringe at the same angle.

Figure I

- There may be a small amount of blood at the injection site. You can press a cotton ball or gauze pad over the injection site. Do not rub the injection site.
- If needed, you may cover the injection site with a bandage (see Figure J).

Figure J

6. Disposing of your used prefilled syringes and needles

- Throw away (discard) the prefilled syringe into an FDA cleared sharps container right away after use (see Figure K). Do not throw away (dispose of) your used needles and syringe in your household trash.

Figure K

- If you do not have an FDA-cleared sharps disposal container, you may use a household container that is:
  - made of a heavy-duty plastic,
  - can be closed with a tight-fitting, puncture-resistant lid, without sharps being able to come out,
  - upright and stable during use,
  - leak-resistant, and
  - properly labeled to warn of hazardous waste inside the container.
- When your sharps disposal container is almost full, you will need to follow your community guidelines for the right way to dispose of your sharps disposal container. There may be state or local laws about how you should throw away used needles and syringes. For more information about safe sharps disposal, and for specific information about sharps disposal in the state that you live in, go to the FDA’s website at: http://www.fda.gov/safesharpsdisposal.
- Do not dispose of your used sharps disposal container in your household trash unless your community guidelines permit this. Do not recycle your used sharps disposal container.

Storing Purified Cortrophin Gel prefilled syringes

- Store Purified Cortrophin Gel prefilled syringes in the carton provided in the refrigerator between 36°F to 46°F (2°C to 8°C).
- Purified Cortrophin Gel prefilled syringes may be stored at room temperature between 68°F to 77°F (20°C to 25°C) for up to 24 hours.
- Keep Purified Cortrophin Gel prefilled syringes in the carton until ready to use.
- Throw away (discard) Purified Cortrophin Gel prefilled syringes right away after use or by the expiration date stamped on the syringe.
- Keep Purified Cortrophin Gel and all medicines out of the reach of children.

Distributed by: ANI Pharmaceuticals, Inc., Baudette, MN 56623
This Instructions for Use has been approved by the U.S. Food and Drug Administration
Revised: February 2025

PACKAGE/LABEL PRINCIPAL DISPLAY PANEL

NDC 62559-860-15
Purified Cortrophin® Gel (repository corticotropin injection USP)
400 USP units/5 mL (80 USP units/mL)
For intramuscular or subcutaneous use.
5 mL, multiple-dose vial
Rx only

PACKAGE/LABEL PRINCIPAL DISPLAY PANEL

NDC 62559-860-11
Purified Cortrophin® Gel (repository corticotropin injection USP)
80 USP units/mL
For intramuscular or subcutaneous use.
1 mL, multiple-dose vial
Rx only

PACKAGE/LABEL PRINCIPAL DISPLAY PANEL

Rx only
NDC 62559-861-35
Purified Cortrophin® Gel (repository corticotropin injection USP)
40 USP units/0.5 mL
For subcutaneous use only.
Single-dose Prefilled Syringe
Remove the Purified Cortrophin Gel carton from the refrigerator 45 minutes prior to injecting.

PACKAGE/LABEL PRINCIPAL DISPLAY PANEL

Rx only
NDC 62559-861-11
Purified Cortrophin® Gel (repository corticotropin injection USP)
80 USP units/mL
For subcutaneous use only.
Single-dose Prefilled Syringe
Remove the Purified Cortrophin Gel carton from the refrigerator 45 minutes prior to injecting.